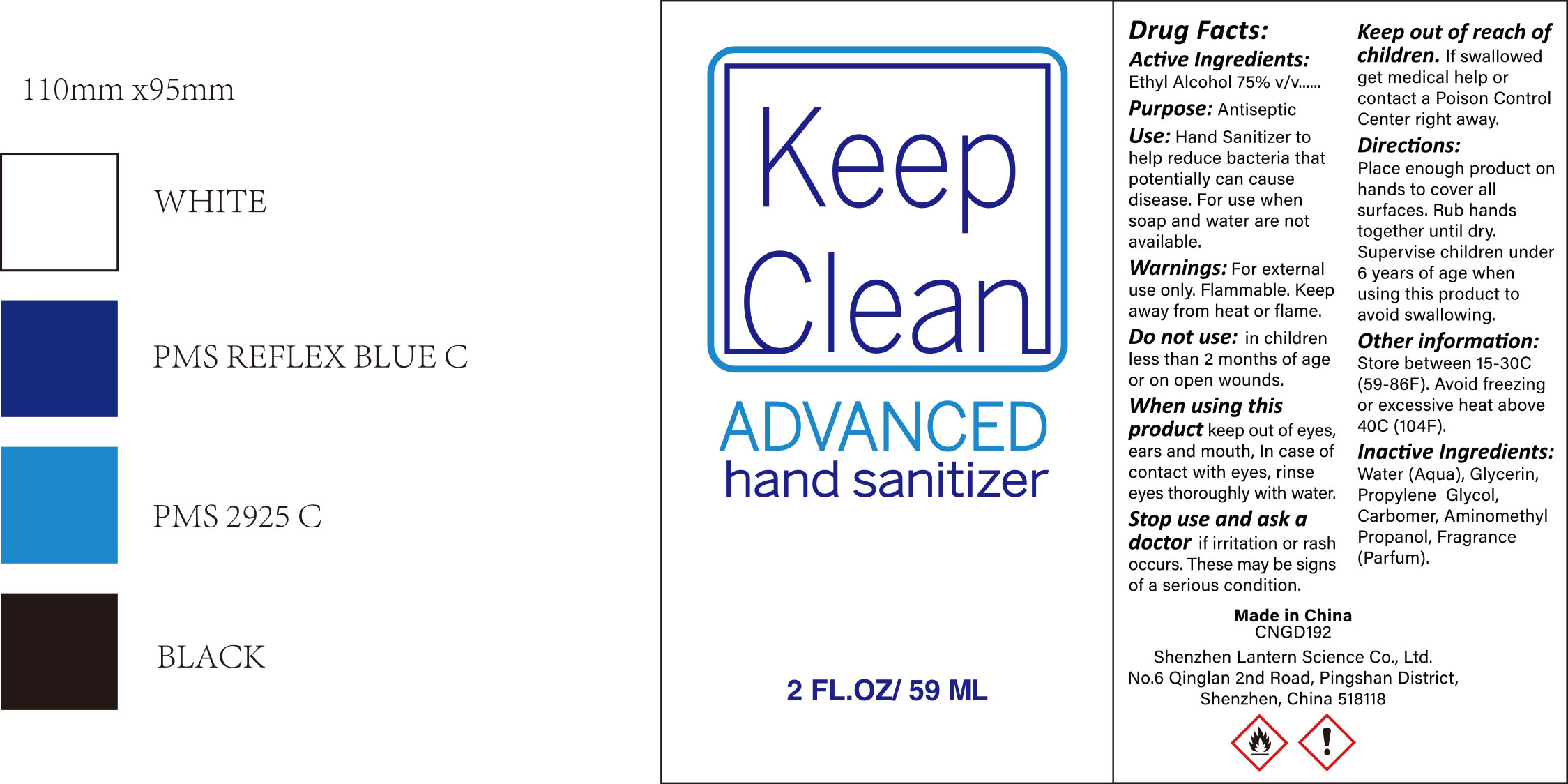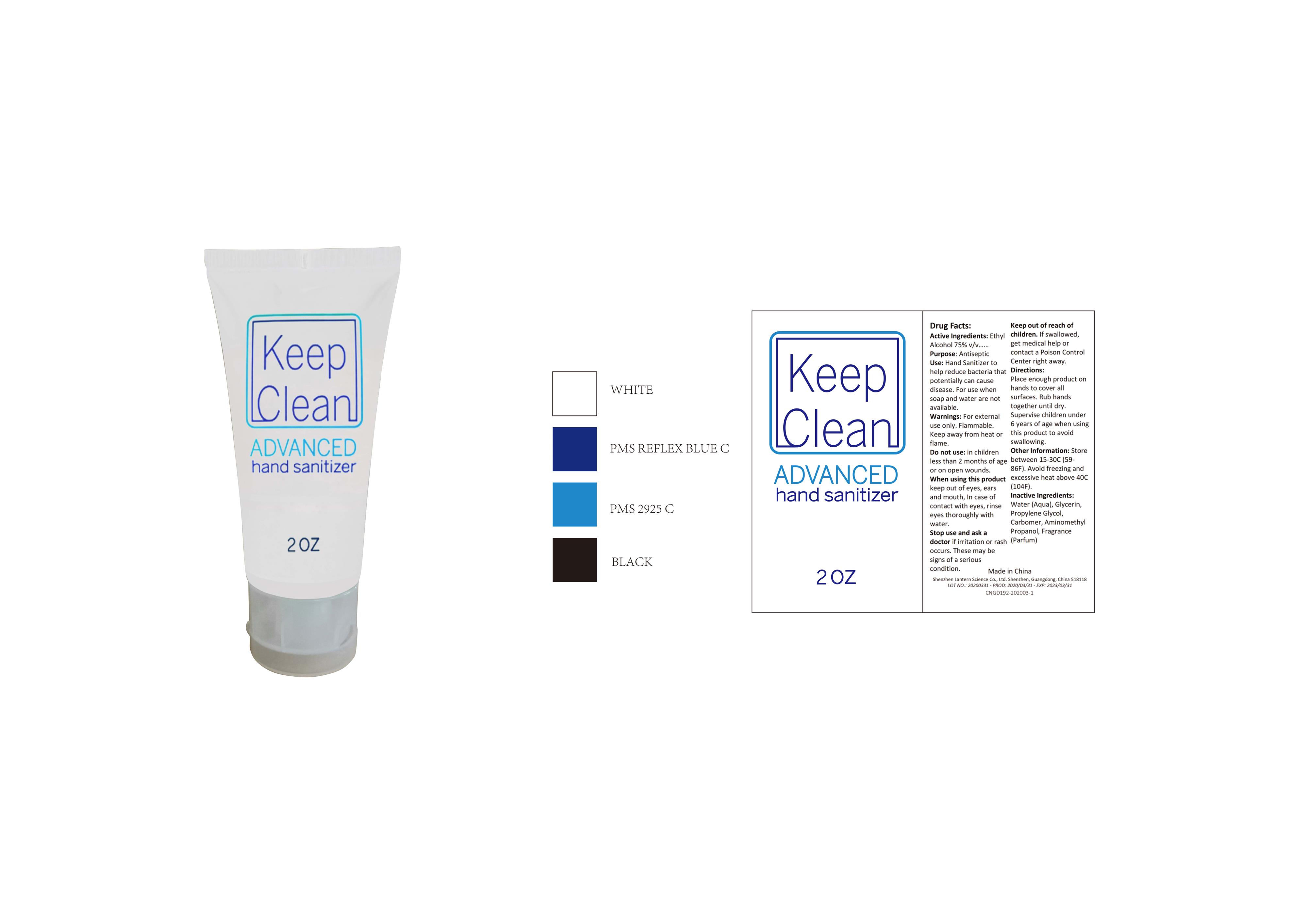 DRUG LABEL: KEEP CLEAN ADVANCED HAND SANITIZER 2OZ
NDC: 54860-149 | Form: LIQUID
Manufacturer: Shenzhen Lantern Scicence Co Ltd
Category: otc | Type: HUMAN OTC DRUG LABEL
Date: 20200920

ACTIVE INGREDIENTS: ALCOHOL 71 g/100 g
INACTIVE INGREDIENTS: PROPYLENE GLYCOL 0.01 g/100 g; LEMON 0.1 g/100 g; CARBOMER 940 0.35 g/100 g; AMINOMETHYLPROPANOL 0.11 g/100 g; WATER 28.42 g/100 g; GLYCERIN 0.01 g/100 g

Keep clean advanced hand sanitizer 2oz

Medicical Ingredient

Medicical Ingredient Purpose

Ethyl Alcohol 75%（V/V） Antiseptic

Features

To decrease bacteria on the skin that could cause disease.

DOSAGE AND ADMINISTRATION

Recommended for repeated use.

use anywhere without water.

Warning

WARNINGS AND PRECAUTIONS

For external use only.

Flammable, keep away from heat and flame.

STOP USE

Discontinue if skin becomes irritated and ask a doctor .

Keep out of reach of children. In case of accidental ingestion, seek professional assistance or contact a poson control center immediately.

Non-Medicinal

Water, Glycerin,Propylene Glycol,Carbomer,,Aminomethyl propanol,Parfum.

Directions

Wet hands thoroughly with product and rub until dry without wiping

For children under 6, use only under adult supervision.

Not recommended for infants.

When using this product

keep out of eyes. In case of contact with eyes, flush thoroughly with water.

Do not inhale or ingest.

Avoid contact with broken skin.

Other information

Do not store above 105F.

May discolor some fabrics.

Harmful to wood finishes and plastics.